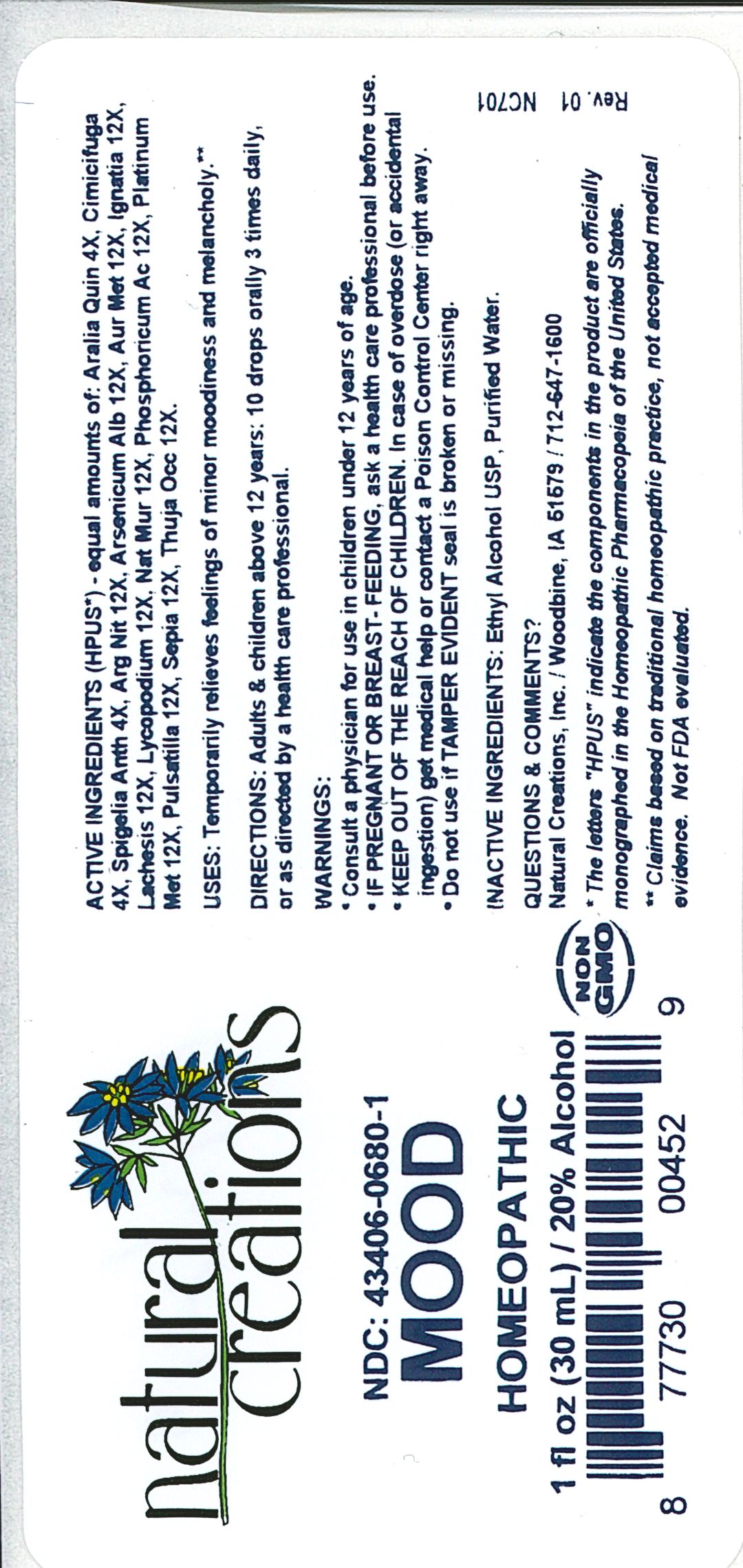 DRUG LABEL: Mood
NDC: 43406-0680 | Form: LIQUID
Manufacturer: Natural Creations, Inc
Category: homeopathic | Type: HUMAN OTC DRUG LABEL
Date: 20251216

ACTIVE INGREDIENTS: AMERICAN GINSENG 4 [hp_X]/1 mL; BLACK COHOSH 4 [hp_X]/1 mL; SPIGELIA ANTHELMIA WHOLE 4 [hp_X]/1 mL; SILVER NITRATE 12 [hp_X]/1 mL; ARSENIC TRIOXIDE 12 [hp_X]/1 mL; GOLD 12 [hp_X]/1 mL; STRYCHNOS IGNATII SEED 12 [hp_X]/1 mL; LACHESIS MUTA VENOM 12 [hp_X]/1 mL; LYCOPODIUM CLAVATUM SPORE 12 [hp_X]/1 mL; SODIUM CHLORIDE 12 [hp_X]/1 mL; PHOSPHORIC ACID 12 [hp_X]/1 mL; PLATINUM 12 [hp_X]/1 mL; PULSATILLA VULGARIS WHOLE 12 [hp_X]/1 mL; SEPIA OFFICINALIS JUICE 12 [hp_X]/1 mL; THUJA OCCIDENTALIS LEAFY TWIG 12 [hp_X]/1 mL
INACTIVE INGREDIENTS: ALCOHOL; WATER

Mood

ACTIVE INGREDIENT

ACTIVE INGREDIENTS (*HPUS) - equal amounts of: Aralia Quin 4X, Cimicifuga 4X, Spigelia Anth 4X, Arg Nit 12X, Arsenicum Alb 12X, Aurum Met 12X, Ignatia Amara 12X, Lachesis 12X, Lycopodium 12X, Nat Mur 12X, Phosphoricum Ac 12X, Platinum Met 12X, Pulsatilla 12X, Sepia 12X, Thuja Occ 12X

INDICATIONS AND USAGE

USES: Temporarily relieves feelings of minor moodiness and melancholy.**

PURPOSE

USES: Temporarily relieves feelings of minor moodiness and melancholy.**

DOSAGE AND ADMINISTRATION

DIRECTIONS: Adults & children above 12 years: 10 drops orally 3 times daily, or as directed by a health care professional.

KEEP OUT OF REACH OF CHILDREN

KEEP OUT OF THE REACH OF CHILDREN. In case of overdose (or accidental ingestion) get medical help or contact a Poison Control Center right away.

WARNINGS:

- Consult a physician for use in children under 12 years of age.
- IF PREGNANT OR BREAST-FEEDING, ask a health care professional before use.
- KEEP OUT OF THE REACH OF CHILDREN. In case of overdose (or accidental ingestion) get medical help or contact a Poison Control Center right away.
- Do not use if TAMPER EVIDENT seal is broken or missing.

INACTIVE INGREDIENTS: Ethyl Alcohol USP, Purified Water

QUESTIONS & COMMENTS?

Natural Creations, Inc. / Woodbine, IA 51579 / 712-647-1600

REFERENCES

*The letters "HPUS" indicate the components in the product are officially monographed in the Homeopathic Pharmacopeia of the United States.

**Claims based on traditional homeopathic practice, not accepted medical evidence. Not FDA evaluated.

PACKAGE LABEL

NDC:43406-0680-1

Mood

HOMEOPATHIC

1 fl oz (30mL) / 20% Alcohol